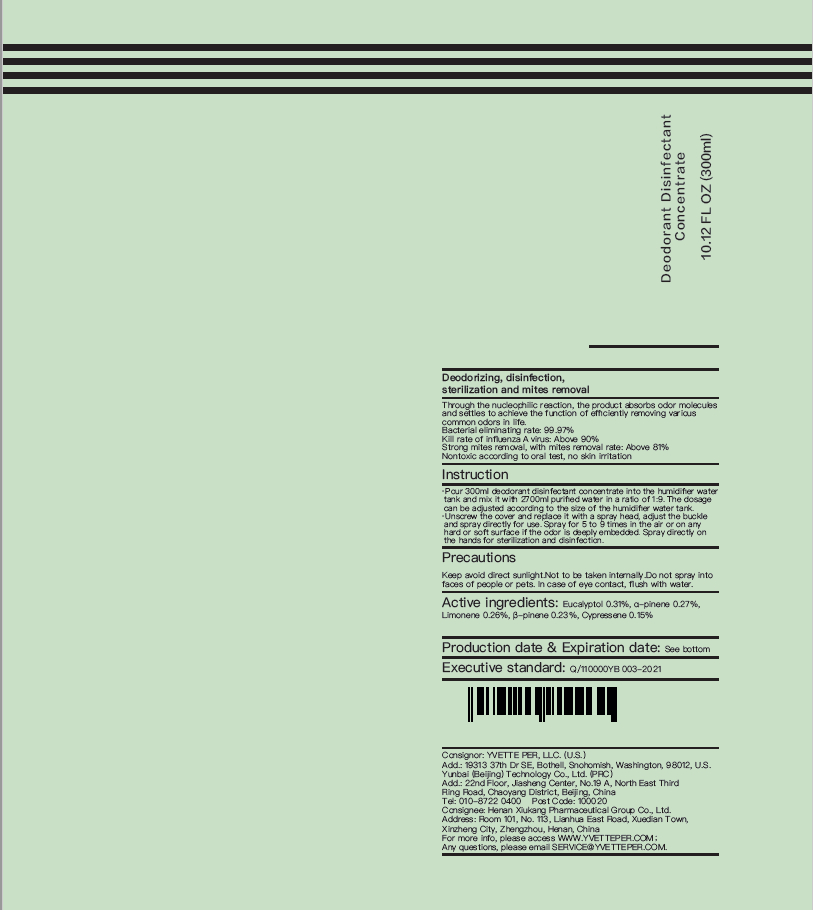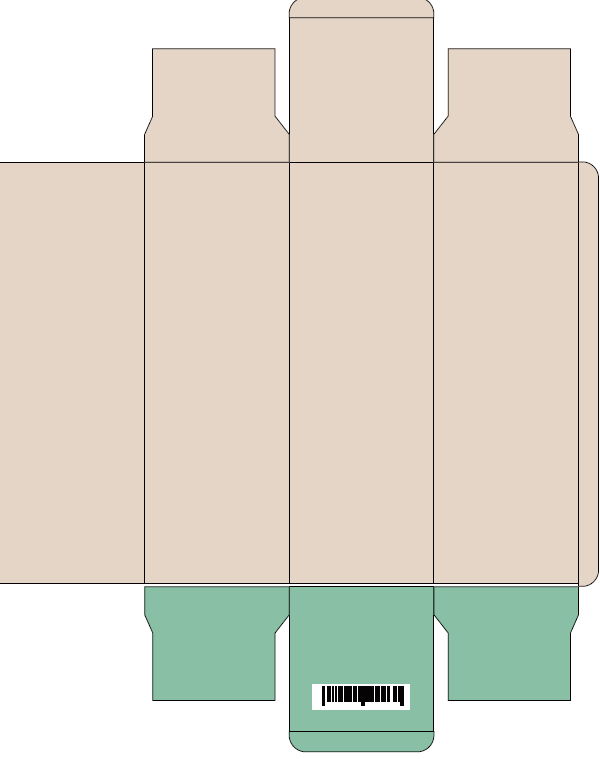 DRUG LABEL: Deodorant disinfectant concentrate
NDC: 82010-001 | Form: LIQUID
Manufacturer: YUNBAI (BEIJING) TECHNOLOGY CO.LTD
Category: otc | Type: HUMAN OTC DRUG LABEL
Date: 20210812

ACTIVE INGREDIENTS: .BETA.-PINENE 0.23 g/100 mL; EUCALYPTOL 0.31 g/100 mL; LIMONENE, (+)- 0.26 g/100 mL; SABINENE 0.15 g/100 mL; .ALPHA.-PINENE 0.27 g/100 mL
INACTIVE INGREDIENTS: WATER; HYDROGENATED CASTOR OIL

ACTIVE INGREDIENT

α-pinene, β-pinene, Sabinene, limonene, eucalyptol

INACTIVE INGREDIENT

hydrogenated castor oil

purified water

PURPOSE

Deodorizing, disinfection,sterilization and mites removal

Steps of use

Pour 300 ml concentrate into the YBS deodorizing and disinfection humidifier, add pure water to the max. water level
(max), or dilute the concentrate according to the concentrate-water proportion of 1: 9; finally, add it into other humidfiers for use.

Unscrew the cover and replace it with a spray head, adjust the buckleand spray directly for use.

INDICATIONS AND USAGE

Strong removal of odor in room and vehicleBacterial eliminating rate: 99.97%
Kill rate of influenza A virus: Above 90%
Strong mites removal, with mites removal rate: Above 81%Nontoxic according to oral test, no skin irritation

Keep out of reach of children.

STORAGE AND HANDLING

Avoid direct sunlight

WARNINGS

Flammable, keep away from fire/flame.For external use only